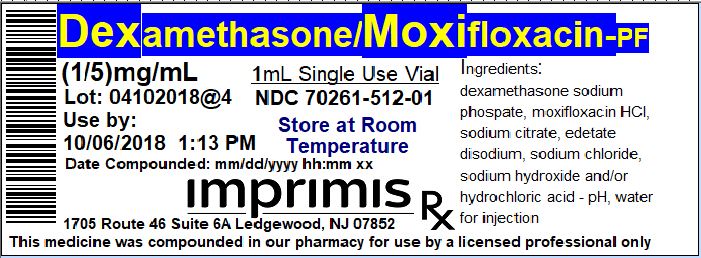 DRUG LABEL: Dex-Moxi PF
NDC: 70261-512 | Form: INJECTION, SOLUTION
Manufacturer: ImprimisRx NJ
Category: prescription | Type: HUMAN PRESCRIPTION DRUG LABEL
Date: 20180508

ACTIVE INGREDIENTS: DEXAMETHASONE SODIUM PHOSPHATE 1 mg/1 mL; MOXIFLOXACIN HYDROCHLORIDE MONOHYDRATE 5 mg/1 mL

STORAGE AND HANDLING

Store at 20° to 25° C (68° to 77° F)